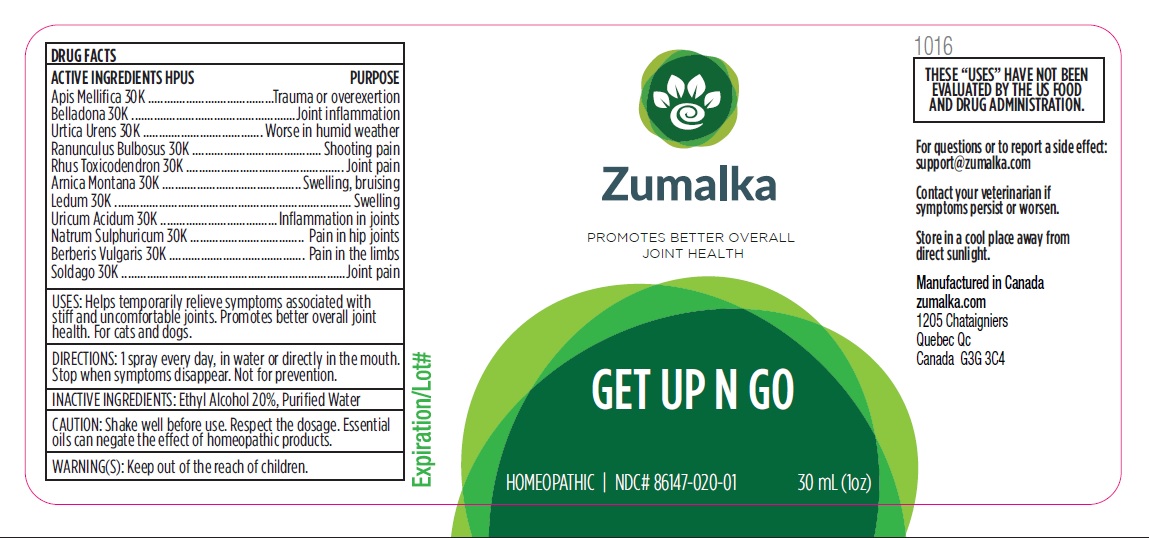 DRUG LABEL: GET UP N GO
NDC: 86147-020 | Form: LIQUID
Manufacturer: Groupe Cyrenne Inc.
Category: homeopathic | Type: OTC ANIMAL DRUG LABEL
Date: 20251120

ACTIVE INGREDIENTS: APIS MELLIFERA 30 [kp_C]/30 mL; ATROPA BELLADONNA 30 [kp_C]/30 mL; URTICA URENS WHOLE 30 [kp_C]/30 mL; BERBERIS VULGARIS WHOLE 30 [kp_C]/30 mL; SOLIDAGO VIRGAUREA FLOWERING TOP 30 [kp_C]/30 mL; SODIUM SULFATE 30 [kp_C]/30 mL; RANUNCULUS BULBOSUS WHOLE 30 [kp_C]/30 mL; TOXICODENDRON PUBESCENS LEAF 30 [kp_C]/30 mL; ARNICA MONTANA FLOWER 30 [kp_C]/30 mL; RHODODENDRON TOMENTOSUM LEAFY TWIG 30 [kp_C]/30 mL; URIC ACID 30 [kp_C]/30 mL
INACTIVE INGREDIENTS: WATER; ALCOHOL

Active ingredient Purpose

Apis Mellifica 30k Trauma or overexertion

Belladonna 30k Joint inflammation

Urtica Urens 30k Worse in humid weather

Ranunculus Bulbosus 30k Shooting pain

Rhus Toxicodendron 30k Joint pain

Arnica Montana 30k Swelling, bruising

Ledum 30k Swelling

Uricum Acidum 30k Inflammation in joints

Berberis Vulgaris 30k Pain in the limbs

Solidago 30k Joint pain

Natrum Sulphuricum 30k Pain in hip joints

Uses

Helps temporarily relieve symptoms associated with still and uncomfortable joints. Promotes better overall joint health. For cats and dogs.

Warnings

Keep out of reach of children.

Direction

1 spray every day, in water or directly in the mouth. Stop when symptoms disappear. Not for prevention.

Inactive ingredient

Ethyl alcohol 20%, purified water

Cautions

Shake well before use. Respect the dosage. Essential oils can negate the effects of homeopathic products. Store in a cool place away from direct sunlight.